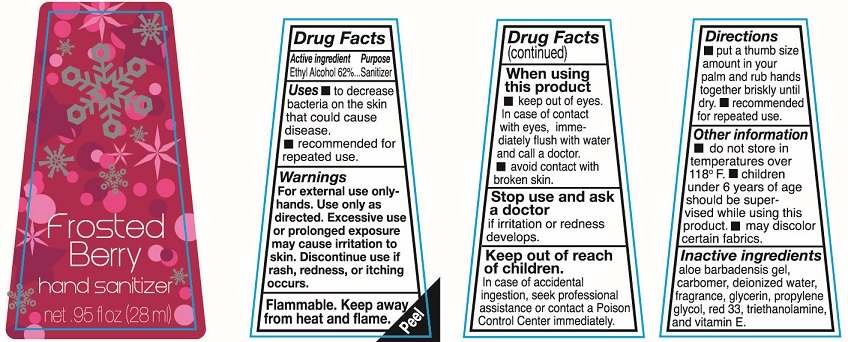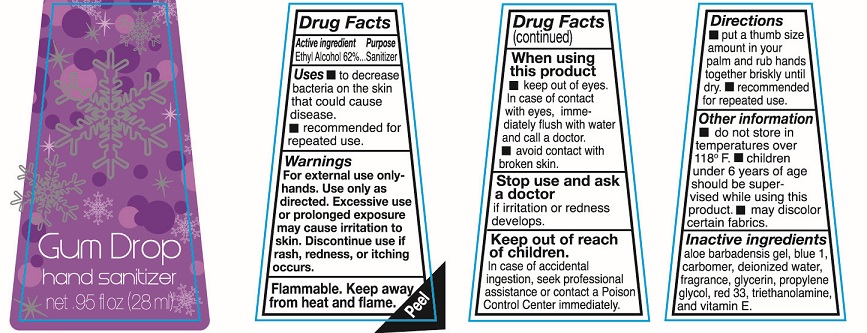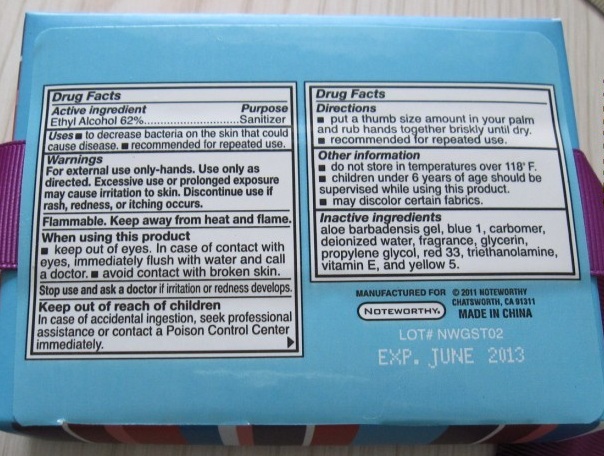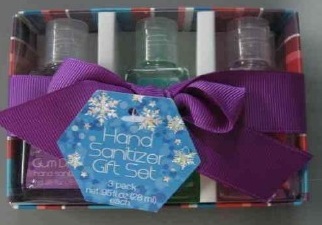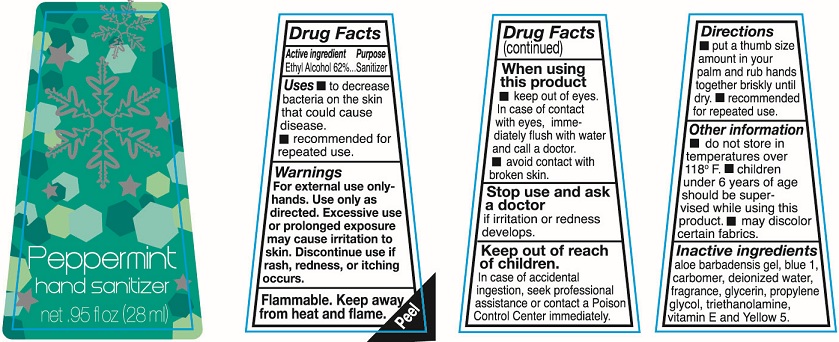 DRUG LABEL: Hand Sanitizer Gift Set
NDC: 75997-030 | Form: KIT | Route: TOPICAL
Manufacturer: Papermates, Inc. DBA Noteworthy
Category: otc | Type: HUMAN OTC DRUG LABEL
Date: 20110706

ACTIVE INGREDIENTS: ALCOHOL 62 mL/100 mL; ALCOHOL 62 mL/100 mL; ALCOHOL 62 mL/100 mL
INACTIVE INGREDIENTS: ALOE; FD&C BLUE NO. 1; WATER; GLYCERIN; PROPYLENE GLYCOL; D&C RED NO. 33; TROLAMINE; ALPHA-TOCOPHEROL; ALOE; FD&C BLUE NO. 1; WATER; GLYCERIN; PROPYLENE GLYCOL; TROLAMINE; ALPHA-TOCOPHEROL; FD&C YELLOW NO. 5; ALOE; WATER; GLYCERIN; PROPYLENE GLYCOL; D&C RED NO. 33; TROLAMINE; ALPHA-TOCOPHEROL

Hand Sanitizer Gift Set

Active Ingredient

Ethyl Alcohol 62%

Purpose

Sanitizer

Uses

To decrease bacteria on the skin that could cause disease.

recommended for repeated use

Warnings

For external use only-hands. Use only as directed. Excessive use or prolonged exposure may cause irritation to skin. Discontinue use if rash redness or itching occurs

Flammable. keep away from heat and flame.

When using this product

keep out of eyes. In case of contact with eyes immediately flush with water and call a doctor

avoid contact with broken skin.

Stop use and ask a doctor if irritation or redness develops.

Keep out of reach of children.

In case of accidental ingestion, seek professional assistance or contact a Poison Control Center immediately.

Directions

put a thumb size amount in your palm and rub hands together briskly until dry. recommended for repeated use.

Other Information

do not store in temperatures over 118F.

Children under 6 years of age should be supervised while using this product.

may discolor certain fabrics.

Inactive Ingredients

aloe barbadensis gel, blue 1, carbomer, deionized water, fragrance, glycerin, propylene glycol, red 33, triethanolamine and vitamin E

PACKAGE LABEL

Gum Drop
Hand sanitizer

net .95fl oz (28ml)

Active Ingredient

Ethyl Alcohol 62%

Purpose

Sanitizer

Uses

To decrease bacteria on the skin that could cause disease.

recommended for repeated use

Warnings

For external use only-hands. Use only as directed. Excessive use or prolonged exposure may cause irritation to skin. Discontinue use if rash redness or itching occurs

Flammable. keep away from heat and flame.

When using this product

keep out of eyes. In case of contact with eyes immediately flush with water and call a doctor

avoid contact with broken skin.

Stop use and ask a doctor if irritation or redness develops.

Keep out of reach of children.

In case of accidental ingestion, seek professional assistance or contact a Poison Control Center immediately.

Directions

put a thumb size amount in your palm and rub hands together briskly until dry. recommended for repeated use.

Other Information

do not store in temperatures over 118F.

Children under 6 years of age should be supervised while using this product.

may discolor certain fabrics.

Inactive Ingredients

aloe barbadensis gel, blue 1, carbomer, deionized water, fragrance, glycerin, propylene glycol, triethanolamine, vitamin E, and Yellow 5

Active Ingredient

Ethyl Alcohol 62%

Purpose

Sanitizer

Uses

To decrease bacteria on the skin that could cause disease.

recommended for repeated use

Warnings

For external use only-hands. Use only as directed. Excessive use or prolonged exposure may cause irritation to skin. Discontinue use if rash redness or itching occurs

Flammable. keep away from heat and flame.

When using this product

keep out of eyes. In case of contact with eyes immediately flush with water and call a doctor

avoid contact with broken skin.

Stop use and ask a doctor if irritation or redness develops.

Keep out of reach of children.

In case of accidental ingestion, seek professional assistance or contact a Poison Control Center immediately.

Directions

put a thumb size amount in your palm and rub hands together briskly until dry. recommended for repeated use.

Other Information

do not store in temperatures over 118F.

Children under 6 years of age should be supervised while using this product.

may discolor certain fabrics.

Inactive Ingredients

aloe barbadensis gel, carbomer, deionized water, fragrance, glycerin, propylene glycol, red 33, triethanolamine and vitamin E

PACKAGE LABEL

Frosted Berry
Hand sanitizer

net .95fl oz (28ml)

PACKAGE LABEL

Peppermint
Hand sanitizer

net .95fl oz (28ml)